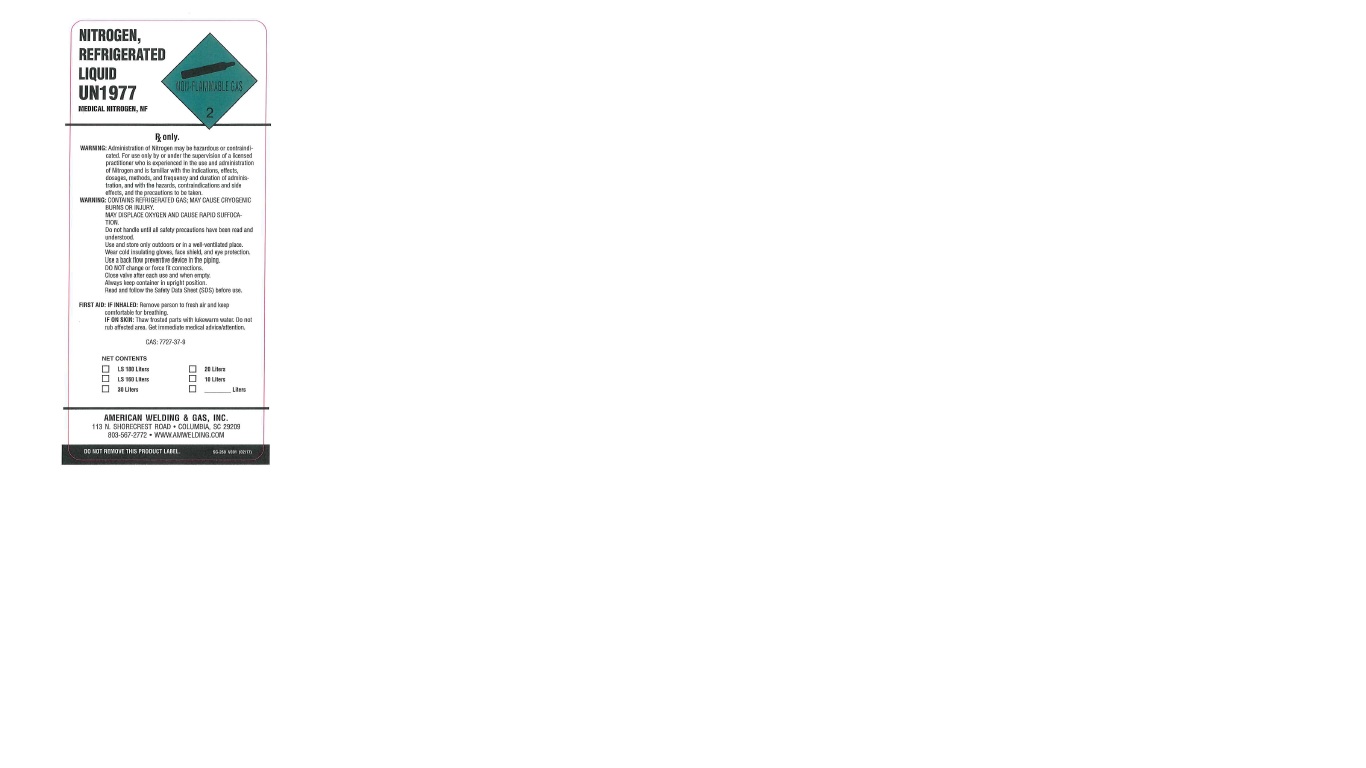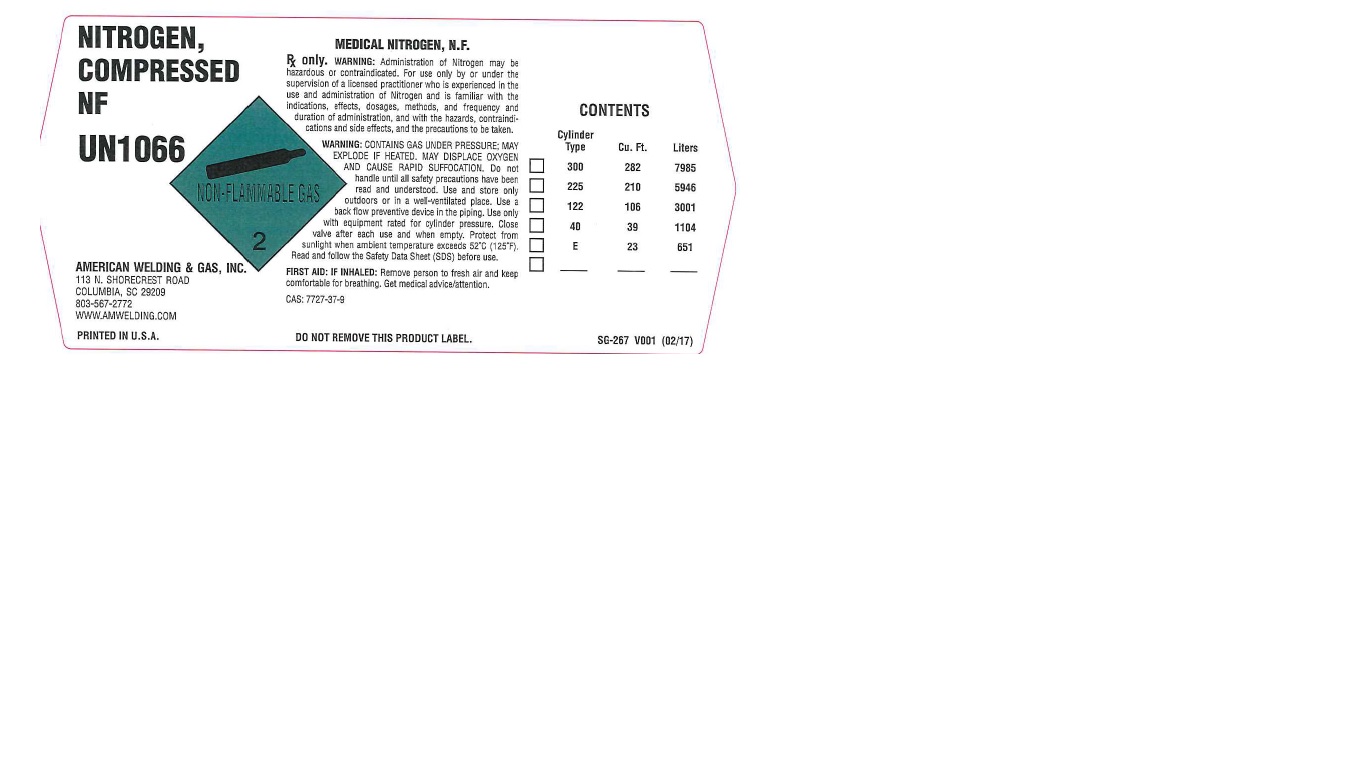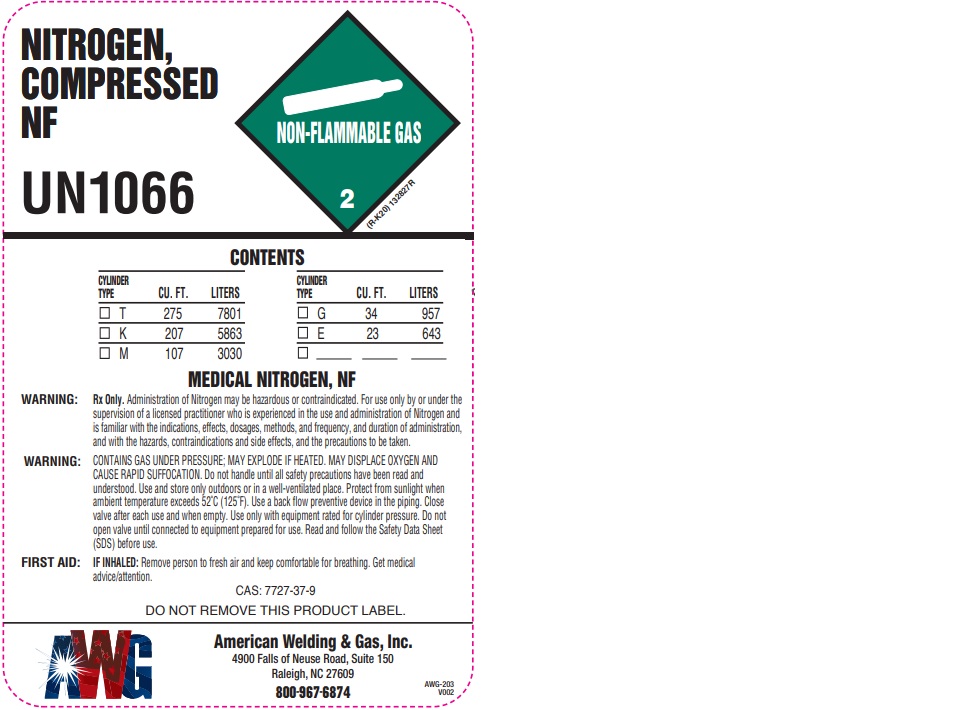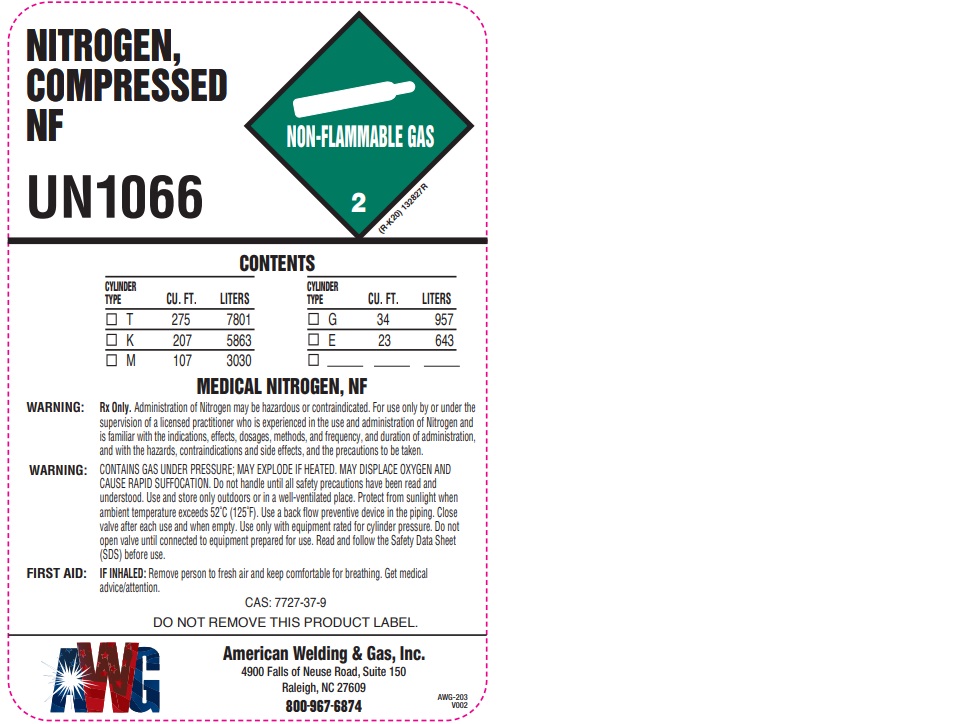 DRUG LABEL: Nitrogen
NDC: 44076-006 | Form: GAS
Manufacturer: American Welding & Gas
Category: prescription | Type: HUMAN PRESCRIPTION DRUG LABEL
Date: 20251028

ACTIVE INGREDIENTS: NITROGEN 990 mL/1 L

Nitrogen

PACKAGE LABEL

NITROGEN, REGRIGERATED LIQUID UN 1977
MEDICAL NITROGEN, NF
RX only.
WARNING: Administration of Nitrogen may be hazardous or contraindicated. For use only by or under the supervision of a licensed practitioner who is experienced in the use and administration of Nitrogen and is familiar with the indications, effects, dosages, methods, and frequency and duration of administration, and with the hazards, contraindications and side effects, and the precautions to be taken.
WARNING: CONTRAINS REGRIGERATED GAS; MAY CAUSE CRYOGENIC BURNS OR INJURY. MAY DISPLACE OXYGEN AND CAUSE RAPID SUFFOCATION.
Do not handle until all safety precautions have been read and understood. Use and store only outdoors or in a well-ventilated place. Wear cold insulating gloves, face shield, and eye protection. Use a back flow preventive device in the piping. DO NOT change or force fit connections. Close valve after each use and when empty. Always keep container in upright position. Read and follow the Safety Data Sheet (SDS) before use.
FIRST AID: IF INHALED: Remove person to fresh air and keep comfortable for breathing. IF ON SKIN: That frosted parts with lukewarm water. Do not rub affected area. Get immediate medical administration.
AMERICAN WELDING & GAS, INC.
113 N. SHORECREST ROAD
COLUMBIA, SC 29209
803-567-2772
WWW.AMWELDING.COM
DO NOT REMOVE THIS PRODUCT LABEL.

PACKAGE LABEL

NITROGEN, COMPRESSED NF UN 1066
MEDICAL NITROGEN, N.F.
RX only. WARNING: Administration of Nitrogen may be hazardous or contraindicated. For use only by or under the supervision of a licensed practitioner who is experienced in the use and administration of Nitrogen and is familiar with the indications, effects, dosages, methods, and frequency and duration of administration, and with the hazards, contraindications and side effects, and the precautions to be taken.
WARNING: CONTAINS GAS UNDER PRESSURE; MAY EXPLODE IF HEATED. MAY DISPLACE OXYGEN AND CAUSE RAPID SUFFOCATION. Do not handle until all safety precautions have been read and understood. Use and store only outdoors or in a well-ventilated piping. Use only with equipment rated for cylinder pressure. Close valve after each use and when empty. Protect from sunlight when ambient temperature exceeds 52 degrees C (125 degrees F). Read and follow the Safety Data Sheet (SDS) before use.
FIRST AID: IF INHALED: Remove person to fresh air and keep comfortable for breathing. Get medical advice/attention.
CAS: 7727-37-9
DO NOT REMOVE THIS PRODUCT LABEL.
SG-267 V001 (02/17)
AMERICAN WELDING & GAS, INC.
113 N. SHORECREST ROAD
COLUMBIA, SC 29209
803-567-2772
WWW.AMWELDING.COM
PRINTED IN THE U.S.A

PACKAGE LABEL

NITROGEN, COMPRESSED NF

UN1066

CONTENTS

CYLINDER TYPE CU. FT. LITERS CYLINDER TYPE CU. FT. LITERS

T 275 7801 G 34 957

K 207 5863 E 23 643

M 107 303

MEDICAL NITROGEN, NF

WARNING: Rx only. Administration of Nitrogen may be hazardous or contraindicated. For use only by or under the supervision of a licensed practitioner who is experienced in the use and administration of Nitrogen and is familiar with the indications, effects, dosages, methods, and frequency, and duration of administration, and with the hazards, contraindications and side effects, and the precautions to be taken.

WARNING: CONTAINS GAS UNDER PRESSURE; MAY EXPLODE IF HEATED. MAY DISPLACE OXYGEN AND CAUSE RAPID SUFFOCATION. Do not handle until all safety precautions have been read and understood. Use and store only outdoors or in a well-ventilated place. Protect from sunlight when ambient temperature exceeds 52 C (125 F). Use a back flow preventive device in the piping. Close after each use and when empty. Use only with equipment rated for cylinder pressure. Do not open valve until connected to equipment prepared for use. Read and follow the Safety Data Sheet (SDS) before use.

FIRST AID: IF INHALED: Remove person to fresh air and keep comfortable for breathing. Get medical advice/attention.

CAS: 7727-37-9

DO NOT REMOVE THIS PRODUCT LABEL.

AWG

American Welding & Gas, Inc.

4900 Falls of Neuse Road, Suite 150

Raleigh, NC 27609

800-967-6874